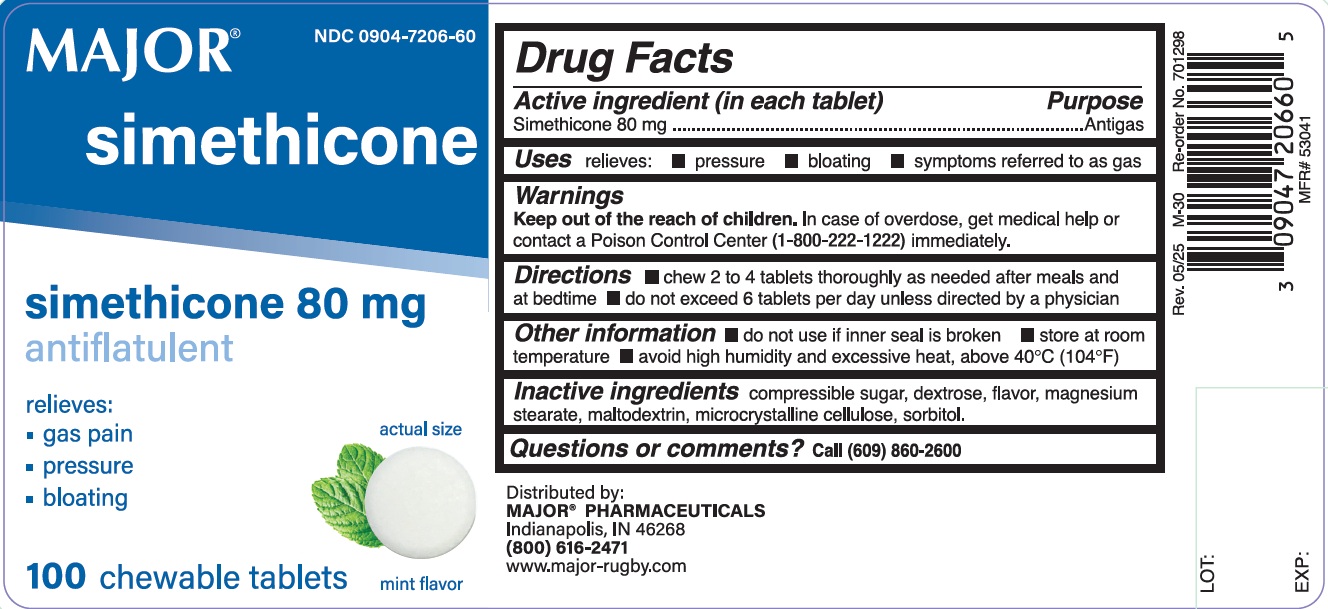 DRUG LABEL: Antiflatulent
NDC: 0904-7206 | Form: TABLET, CHEWABLE
Manufacturer: Major Pharmaceuticals
Category: otc | Type: Human OTC Drug Label
Date: 20251203

ACTIVE INGREDIENTS: DIMETHICONE 80 mg/1 1
INACTIVE INGREDIENTS: SUGARCANE; MALTODEXTRIN; DEXTROSE, UNSPECIFIED FORM; MAGNESIUM STEARATE; MICROCRYSTALLINE CELLULOSE; SORBITOL

Major Simethicone

ACTIVE INGREDIENT(in each tablet)

Simethicone 80 mg

PURPOSE

Antigas

USE(S)

relieves:

- pressure
- bloating
- symptoms referred to as gas

WARNINGS

.

KEEP OUT OF REACH OF CHILDREN

In case of overdose, get medical help or contact a Poison Control Center (1-800-222-1222) immediately.

DIRECTIONS

- chew 2 to 4 tablets thoroughly as needed after meals and at bedtime
- do not exceed 6 tablets per day unless directed by a physician

OTHER INFORMATION

- do not use if inner seal is broken
- store at room temperature
- avoid high humidity and excessive heat, above 40oC (104oF)

INACTIVE INGREDIENTS

compressible sugar, dextrose, flavor, magnesium stearate, maltodextrin, microcrystalline cellulose, sorbitol.

QUESTIONS

Call (800) 616-2471

PRINCIPAL DISPLAY PANEL

NDC 0904-7206-60
MAJOR

Simethicone

Simethicone 80 mg

antiflatulent

relieves:

- gas pain
- pressure
- bloating

100 Chewable Tablets